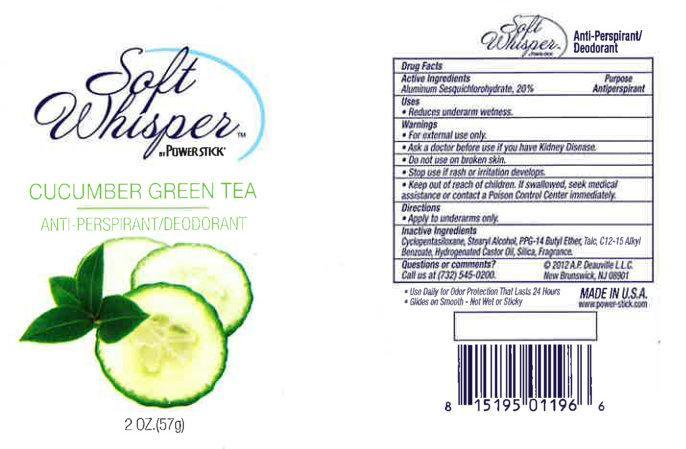 DRUG LABEL: Soft Whisper Cucumber Green Tea
NDC: 42913-010 | Form: STICK
Manufacturer: A.P. Deauville, LLC
Category: otc | Type: HUMAN OTC DRUG LABEL
Date: 20240715

ACTIVE INGREDIENTS: ALUMINUM SESQUICHLOROHYDRATE 200 mg/1 g
INACTIVE INGREDIENTS: CYCLOMETHICONE 5; STEARYL ALCOHOL; ALKYL (C12-15) BENZOATE; BUTYL ETHER; TALC; HYDROGENATED CASTOR OIL; SILICON DIOXIDE

Soft Whisper Cucumber Green Tea

Active ingredient

Aluminum Sesquichlorohydrate 20%

Purpose

Antiperspirant

Use

Reduces underarm wetness

Warnings

For external use only

if you have kidney disease Ask a doctor before use

on broken skin Do not use

rash or irritation occurs Stop use if

Keep out of reach of children.

If swallowed, get medical help or contact a Poison Control Center immediately.

Directions

Apply to underarms only.

Inactive ingredients

CYCLOPENTASILOXANE, STEARYL ALCOHOL, C12-15 ALKYL BENZOATE, PPG-14 BUTYL ETHER, TALC, HYDROGENATED CASTOR OIL, SILICA, Fragrance.

Questions or Comments?

Call us at (732) 545-0200

2011 A.P.Deauville LLC

New Brunswick, NJ 08901

Soft Whisper Cucumber Green Tea Package Label

Soft Whisper by Powerstick

Cucumber Green Tea

ANTI-PERSPIRANT/DEODORANT

NET WT. 2 OZ. (57g)